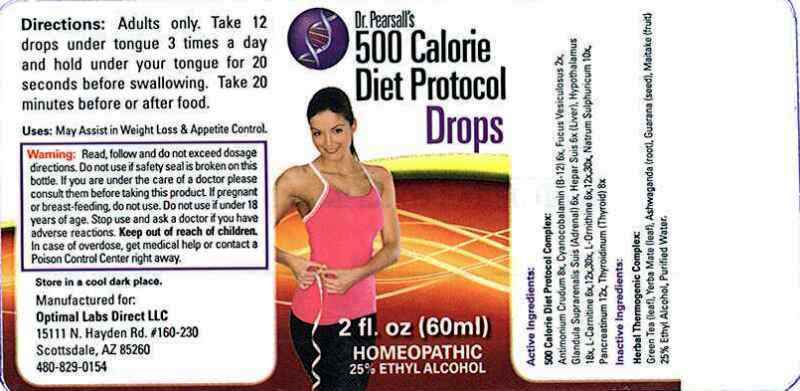 DRUG LABEL: Dr. Pearsalls 500 Calorie Diet
NDC: 57520-1047 | Form: LIQUID
Manufacturer: Apotheca Company
Category: homeopathic | Type: HUMAN OTC DRUG LABEL
Date: 20120202

ACTIVE INGREDIENTS: FUCUS VESICULOSUS 2 [hp_X]/1 mL; CYANOCOBALAMIN 6 [hp_X]/1 mL; SUS SCROFA ADRENAL GLAND 6 [hp_X]/1 mL; PORK LIVER 6 [hp_X]/1 mL; LEVOCARNITINE 6 [hp_X]/1 mL; ORNITHINE 6 [hp_X]/1 mL; ANTIMONY TRISULFIDE 8 [hp_X]/1 mL; THYROID, PORCINE 8 [hp_X]/1 mL; SODIUM SULFATE 10 [hp_X]/1 mL; PANCRELIPASE 12 [hp_X]/1 mL; SUS SCROFA HYPOTHALAMUS 18 [hp_X]/1 mL
INACTIVE INGREDIENTS: GREEN TEA LEAF; ILEX PARAGUARIENSIS LEAF; WITHANIA SOMNIFERA ROOT; PAULLINIA CUPANA SEED; MAITAKE; WATER; ALCOHOL

Dr. Pearsall's 500 Calorie Diet Protocol Drops

ACTIVE INGREDIENT

ACTIVE INGREDIENTS: Fucus vesiculosus 2X, Cyanocolalamin (B12) 6X, Glandula suprarenalis suis (adrenal) 6X, Hepar suis (liver) 6X, L-Carnitine 6X, 12X, 30X, L-Ornithine 6X, 12X, 30X, Antimonium crudum 8X, Thyroidinum (suis) (thyroid) 8X, Natrum sulphuricum 10X, Pancreatinum 12X, Hypothalamus (suis) 18X.

PURPOSE

USES: Assist in Weight Loss and Appetite Control

WARNINGS

WARNINGS: Read, follow and do not exceed dosage directions.

Do not use if safety seal is broken on this bottle.

If you are under the care of a doctor, please consult them before taking this product.

If pregnant or breast-feeding, do not use.

Do not use if under 18 years of age.

Stop use and ask a doctor if you have adverse reactions.

Keep out of reach of children. In case of overdose, get medical help or contact a Poison Control Center right away.

Store in a cool, dark place.

DOSAGE AND ADMINISTRATION

DIRECTIONS: Adults only. Take 12 drops under the tongue 3 times a day and hold under your tongue for 20 seconds before swallowing. Take 20 minutes before or after food.

INACTIVE INGREDIENT

INACTIVE INGREDIENTS: Green tea (leaf), Yerba mate (leaf), Ashwagandha (root), Guarana (seed), Maitake (fruit, Purified water, Ethanol 25%.

KEEP OUT OF REACH OF CHILDREN. In case of overdose, get medical help or contact a Poison Control Center right away.

INDICATIONS AND USAGE

USES: May Assist in Weight Loss and Appetite Control.

QUESTIONS

Manufactured for:

Optimal Labs Direct LLC

15111 N. Hayden Rd. #160-230

Scottsdale, AZ 85260

480-829-0154

PACKAGE LABEL

DR. PEARSALLS

500 CALORIE DIET PROTOCOL DROPS

22 fl. oz (60 ml)

HOMEOPATHIC